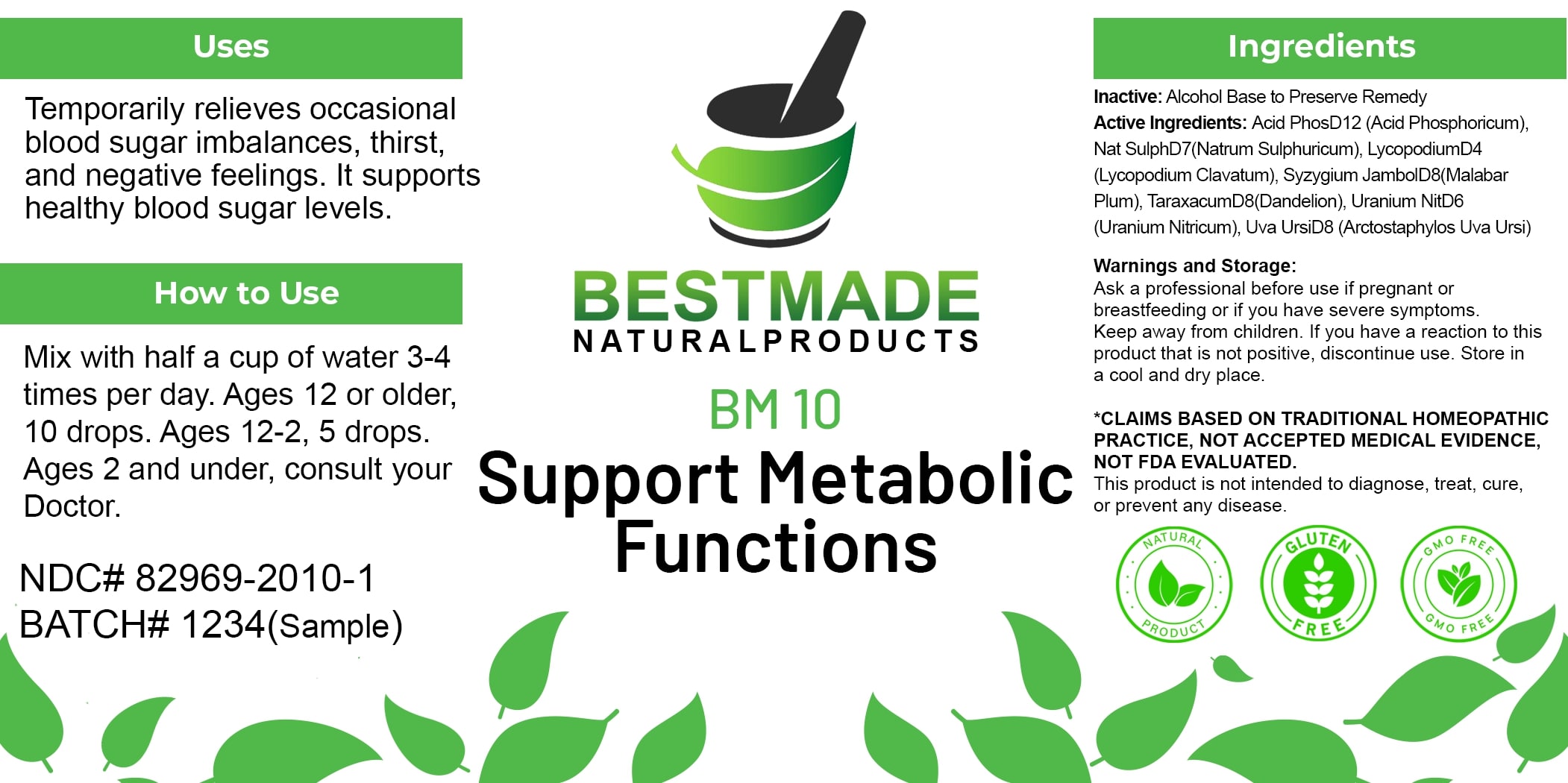 DRUG LABEL: Bestmade Natural Products BM10
NDC: 82969-2010 | Form: LIQUID
Manufacturer: Bestmade Natural Products
Category: homeopathic | Type: HUMAN OTC DRUG LABEL
Date: 20250122

ACTIVE INGREDIENTS: LYCOPODIUM CLAVATUM SPORE 30 [hp_C]/30 [hp_C]; SYZYGIUM CUMINI SEED 30 [hp_C]/30 [hp_C]; TARAXACUM OFFICINALE 30 [hp_C]/30 [hp_C]; ARCTOSTAPHYLOS UVA-URSI LEAF 30 [hp_C]/30 [hp_C]; SODIUM SULFATE 30 [hp_C]/30 [hp_C]; URANYL NITRATE HEXAHYDRATE 30 [hp_C]/30 [hp_C]; PHOSPHORIC ACID 30 [hp_C]/30 [hp_C]
INACTIVE INGREDIENTS: ALCOHOL 30 [hp_C]/30 [hp_C]

BM10

DOSAGE AND ADMINISTRATION

How to Use

Mix with half a cup of water 3-4 times per day.

Ages 12 or older: 10 drops
Ages 2-12: 5 drops
Ages 2 and under: Consult your doctor.

Uses

Temporarily relieves occasional blood sugar imbalances, thirst, and negative feelings. It supports healthy blood sugar levels.

*CLAIMS BASED ON TRADITIONAL HOMEOPATHIC PRACTICE, NOT ACCEPTED MEDICAL EVIDENCE, NOT FDA EVALUATED.
This product is not intended to diagnose, treat, cure, or prevent any disease.

INACTIVE INGREDIENT

Ingredients

Inactive: Alcohol Base to Preserve Remedy

Active Ingredients:

Acid PhosD12 (Acid Phosphoricum)
Nat SulphD7 (Natrum Sulphuricum)
LycopodiumD4 (Lycopodium Clavatum)
Syzygium JambolD8 (Malabar Plum)
TaraxacumD8 (Dandelion)
Uranium NitD6 (Uranium Nitricum)
Uva UrsiD8 (Arctostaphylos Uva Ursi)

KEEP OUT OF REACH OF CHILDREN

Warnings and Storage

Ask a professional before use if pregnant or breastfeeding or if you have severe symptoms. Keep away from children. If you have a reaction to this product that is not positive, discontinue use. Store in a cool and dry place.

Uses

Temporarily relieves occasional blood sugar imbalances, thirst, and negative feelings. It supports healthy blood sugar levels.

*CLAIMS BASED ON TRADITIONAL HOMEOPATHIC PRACTICE, NOT ACCEPTED MEDICAL EVIDENCE, NOT FDA EVALUATED.
This product is not intended to diagnose, treat, cure, or prevent any disease.

Warnings and Storage

Ask a professional before use if pregnant or breastfeeding or if you have severe symptoms. Keep away from children. If you have a reaction to this product that is not positive, discontinue use. Store in a cool and dry place.

*CLAIMS BASED ON TRADITIONAL HOMEOPATHIC PRACTICE, NOT ACCEPTED MEDICAL EVIDENCE, NOT FDA EVALUATED.
This product is not intended to diagnose, treat, cure, or prevent any disease.

Entire package label